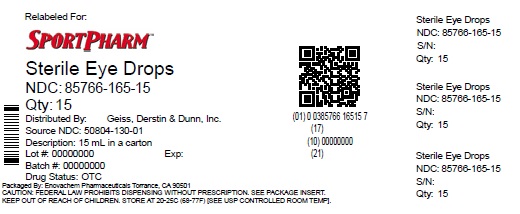 DRUG LABEL: GoodSense Eye Drops Advanced Relief Moisturizer
NDC: 85766-165 | Form: SOLUTION
Manufacturer: Sportpharm LLC
Category: otc | Type: HUMAN OTC DRUG LABEL
Date: 20260206

ACTIVE INGREDIENTS: POLYETHYLENE GLYCOL 400 1 g/100 mL; TETRAHYDROZOLINE HYDROCHLORIDE 0.05 g/100 mL; POVIDONE 1 g/100 mL; DEXTRAN 70 0.1 g/100 mL
INACTIVE INGREDIENTS: BENZALKONIUM CHLORIDE; BORIC ACID; SODIUM BORATE; EDETATE DISODIUM; WATER; SODIUM CHLORIDE

GoodSense Eye Drops Advanced Relief Moisturizer (PLD)

Active Ingredients

Dextran 70.....0.1%

Polyethylene glycol 400.....1%

Povidone.....1%

tetrahydrozoline HCl.....0.05%

Purposes

Dextran 70.....Lubricant

Polyethylene glycol 400.....Lubricant

Povidone.....Lubricant

Tetrahydrozoline HCl .....Redness reliever

Uses

- relieves redness of the eye due to minor eye irritations
- as a lubricant to prevent further irritation or to relieve dryness of the eye

Warnings

For external use only

Ask a doctor before use if you havenarrow angle glaucoma

Stop use and ask a doctor if you experience

- eye pain
- changes in vision
- continued redness or irritation of the eye, or if the condition worsens or persists for more than 72 hours

When using this product

- pupils may become enlarged temporarily
- to avoid contamination, do not touch tip of container to any surface. Replace cap after using.
- if solution changed color or becomes cloudy, do not use
- overuse may produce increased redness of the eye
- remove contact lens before using

PREGNANCY OR BREAST FEEDING

If pregnant or breast-feeding ,ask a health professional before use.

Keep out of reach of children. If swallowed, get medical help or contact a Poison control Center (1-800-111-1222) right away.

Directions

Instill 1 to 2 drops in the affected eye(s) up to 4 times daily.

Inactive ingredients

benzalkonium chloride, boric acid, edetate disodium, purified water, sodium borate, and sodium chloride